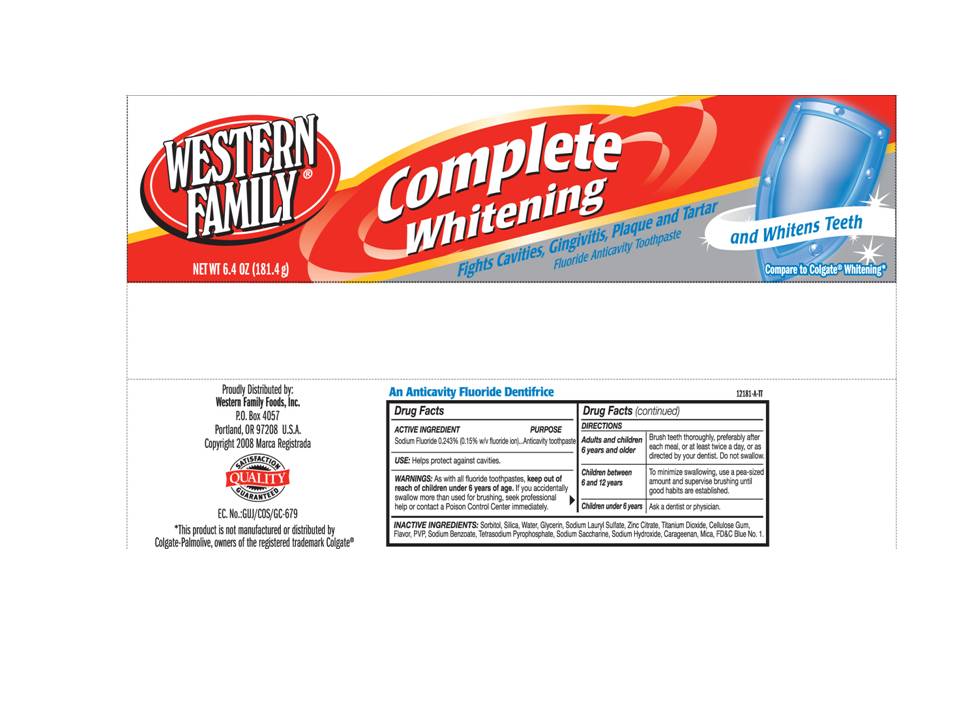 DRUG LABEL: Western Family Complete Whitening
NDC: 55312-003 | Form: PASTE, DENTIFRICE
Manufacturer: Western Family Foods, Inc
Category: otc | Type: HUMAN OTC DRUG LABEL
Date: 20110110

ACTIVE INGREDIENTS: Sodium Fluoride 2.43 mg/1 g
INACTIVE INGREDIENTS: SORBITOL; SILICON DIOXIDE; WATER; GLYCERIN; SODIUM LAURYL SULFATE; ZINC CITRATE; TITANIUM DIOXIDE; CARBOXYMETHYLCELLULOSE SODIUM; SODIUM BENZOATE; SODIUM PYROPHOSPHATE; SACCHARIN SODIUM; SODIUM HYDROXIDE; CARRAGEENAN ; MICA; FD&C BLUE NO. 1

Western Family Complete Whitening Fluoride Anticavity Toothpaste

Active Ingredient

Sodium Fluoride 0.243% (0.15% w/v fluoride ion)...Anticavity toothpaste

INDICATIONS AND USAGE

Helps protect against cavities.

WARNINGS

As with all fluoride toothpastes, keep out of reach of children under 6 years of age. If you accidentally swallow more than used for brushing, seek professional help or contact a Poison Control Center immediately.

DOSAGE AND ADMINISTRATION

Adults and children Brush teeth throughly, preferably after
6 years and older each meal, or at least twice a day, or as
directed by your dentist. Do not swallow.

Children between To minimize swallowing, use a pea-sized
6 and 12 years amount and supervise brushing until
good habits are established.

Children under 6 years Ask a dentist or physician.

Inactive Ingredients:

Sorbitol, Silica, Water, Glycerin, Sodium Lauryl Sulfate, Zinc Citrate, Titanium Dioxide, Cellulose Gum, Flavor, PVP, Sodium Benzoate, Tetrasodium Pyrophosphate, Sodium Saccharine, Sodium Hydroxide, Carageenan, Mica, FDC Blue No.1.